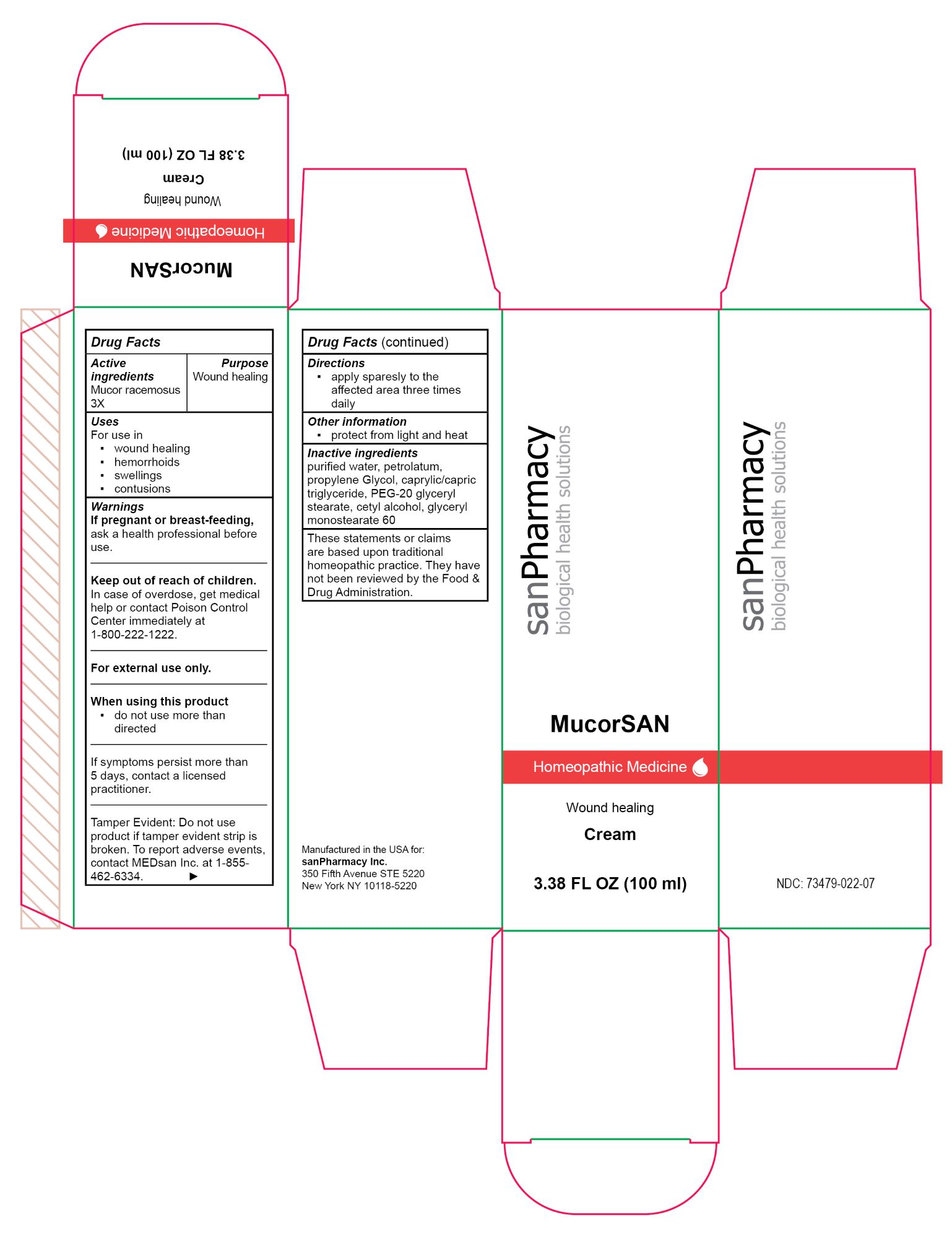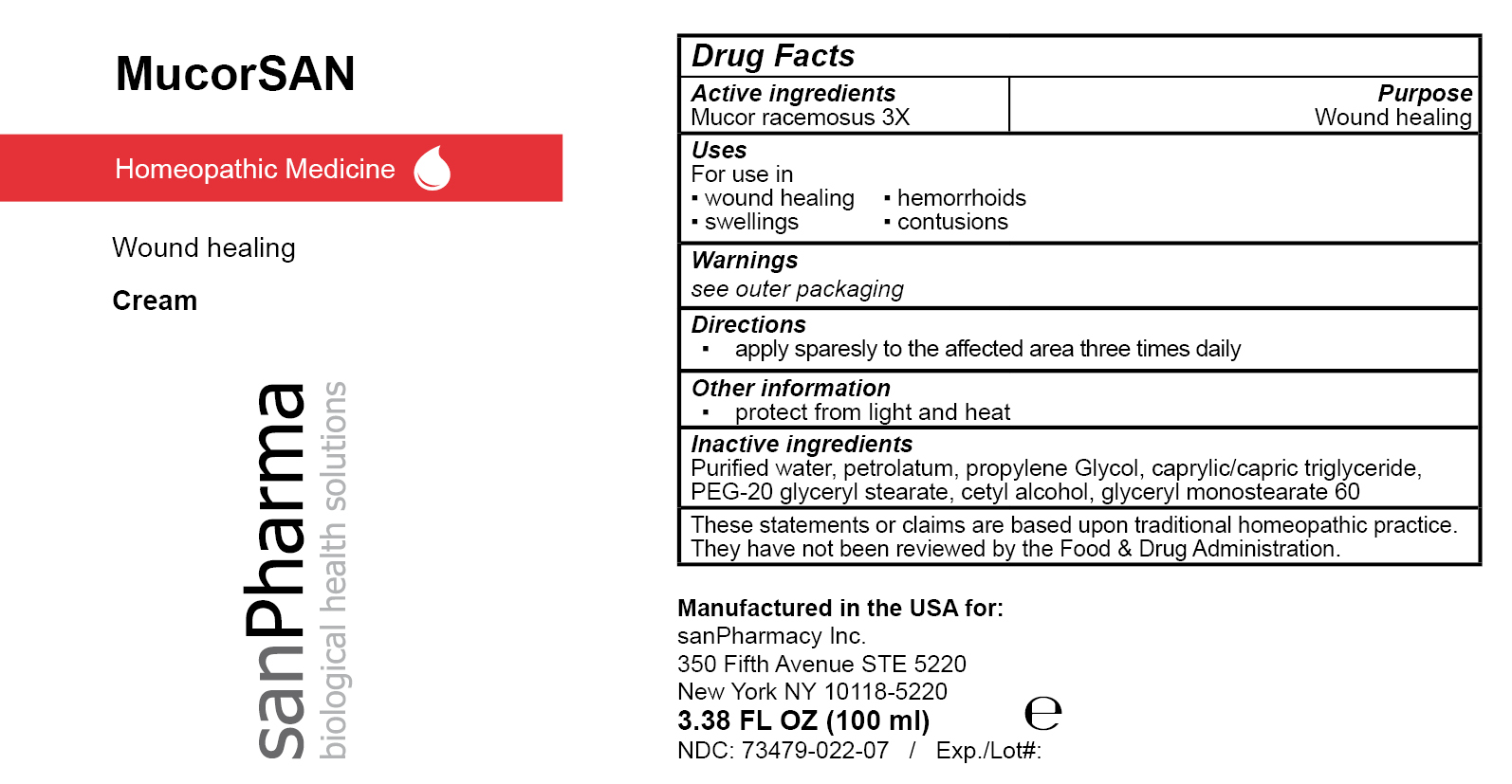 DRUG LABEL: MucorSAN
NDC: 73479-022 | Form: CREAM
Manufacturer: sanPharmacy Inc.
Category: homeopathic | Type: HUMAN OTC DRUG LABEL
Date: 20240430

ACTIVE INGREDIENTS: MUCOR RACEMOSUS 3 [hp_X]/100 mL
INACTIVE INGREDIENTS: GLYCERYL MONOSTEARATE; PROPYLENE GLYCOL; MEDIUM-CHAIN TRIGLYCERIDES; PEG-20 GLYCERYL STEARATE; CETYL ALCOHOL; PETROLATUM; WATER

MucorSAN Cream

Indications

Wound healing

Purpose

Wound healing

Dosage

apply sparesly to the affected area three times daily

Active ingredients

Mucor racemosus 3X

Inactive ingeredients

purified water, petrolatum, propylene Glycol, caprylic/capric triglyceride, PEG-20 glyceryl stearate, cetyl alcohol, glyceryl monostearate 60

Warnings

If pregnant or breast-feeding, ask a health professional before use.
______________________________
Keep out of reach of children. In case of ingestion call Poison Control Center hotline immediately at 1-800-222-1222.
______________________________
For external use only.
______________________________
When using this product
▪ do not use more than directed
______________________________
If symptoms persist more than 5 days, contact a licensed practitioner.
______________________________
Tamper Evident: Do not use product if tamper evident strip is broken. To report adverse events, contact MEDsan Inc. at 1-855-462-6334.

Keep out of reach of children. In case of ingestion call Poison Control Center hotline immediately at 1-800-222-1222

Manufactured in the USA for:
sanPharmacy Inc.
350 Fifth Avenue STE 5220
New York NY 10118-5220

Liability statement

These statements or claims are based upon traditional homeopathic practice. They have not been reviewed by the Food & Drug Administration

STORAGE AND HANDLING

protect from light and heat

PACKAGE LABEL

MucorSAN

Homeopathic Medicine

Wound healing

Cream

3.38 FL OZ (100 ml)

sanPharmacy

biological health solutions